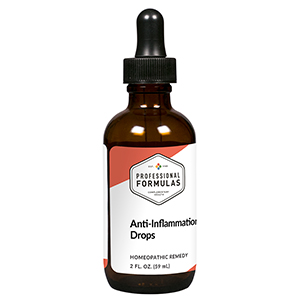 DRUG LABEL: Anti-Inflammation Drops
NDC: 63083-2005 | Form: LIQUID
Manufacturer: Professional Complementary Health Formulas
Category: homeopathic | Type: HUMAN OTC DRUG LABEL
Date: 20190815

ACTIVE INGREDIENTS: BRYONIA ALBA ROOT 3 [hp_X]/59 mL; ECHINACEA PURPUREA WHOLE 3 [hp_X]/59 mL; APIS MELLIFERA 6 [hp_X]/59 mL; ARNICA MONTANA WHOLE 6 [hp_X]/59 mL; AMARYLLIS BELLADONNA WHOLE 6 [hp_X]/59 mL; FERROSOFERRIC PHOSPHATE 6 [hp_X]/59 mL; CALCIUM SULFIDE 6 [hp_X]/59 mL; ARSENIC TRIOXIDE 8 [hp_X]/59 mL; LACHESIS MUTA VENOM 8 [hp_X]/59 mL; CORTISONE ACETATE 12 [hp_X]/59 mL; MERCURIUS SOLUBILIS 12 [hp_X]/59 mL
INACTIVE INGREDIENTS: ALCOHOL; WATER

C5

ACTIVE INGREDIENTS

Bryonia 3X
Echinacea purpurea 3X
Apis mellifica 6X
Arnica montana 6X
Belladonna 6X
Ferrum phosphoricum 6X
Hepar sulphuris calcareum 6X
Arsenicum album 8X
Lachesis mutus 8X
Cortisone aceticum 12X
Mercurius solubilis 12X

QUESTIONS

Professional Formulas

PO Box 2034 Lake Oswego, OR 97035

INDICATIONS

For the temporary relief of minor pain, redness, swelling, or stiffness of joints, muscles, or connective tissues.*

PURPOSE

*Claims based on traditional homeopathic practice, not accepted medical evidence. Not FDA evaluated.

WARNINGS

In case of overdose, get medical help or contact a poison control center right away.

Keep out of the reach of children.

PREGNANCY OR BREAST FEEDING

If pregnant or breastfeeding, ask a healthcare professional before use.

DIRECTIONS

Place drops under tongue 30 minutes before/after meals. Adults and children 12 years and over: Take 10 drops up to 3 times per day for up to 6 weeks. For immediate onset of symptoms, take 10 to 15 drops every 15 minutes up to 3 hours. For less severe symptoms, take 10-15 drops hourly up to 8 hours. Consult a physician for use in children under 12 years of age.

OTHER INFORMATION

Tamper resistant. If seal is broken, do not use. After opening, close container tightly and store at room temperature away from heat.

INACTIVE INGREDIENTS

20% ethanol, purified water.

LABEL

Est 1985

Professional Formulas

Complementary Health

Anti-Inflammation Drops

Homeopathic Remedy

2 FL. OZ. (59 mL)